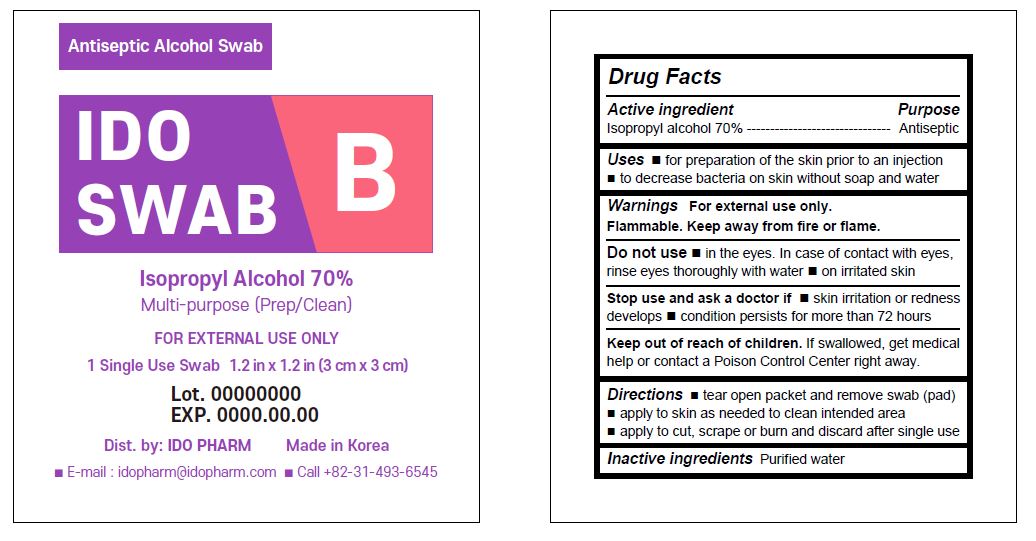 DRUG LABEL: IDOSWAB B
NDC: 77039-027 | Form: LIQUID
Manufacturer: IDO PHARM
Category: otc | Type: HUMAN OTC DRUG LABEL
Date: 20260105

ACTIVE INGREDIENTS: ISOPROPYL ALCOHOL 70 mL/100 mL
INACTIVE INGREDIENTS: WATER

ACTIVE INGREDIENT

isopropyl alcohol 70%

INACTIVE INGREDIENT

Water

PURPOSE

 for preparation of the skin prior to an injection
 to decrease bacteria on skin without soap and water

Keep out of reach of children

INDICATIONS AND USAGE

 tear open packet and remove swab (pad)
 apply to skin as needed to clean intended area
 apply to cut, scrape or burn and discard after single use

WARNINGS

Flammable, keep away from fire and flames
For external use only

DOSAGE AND ADMINISTRATION

For external use only